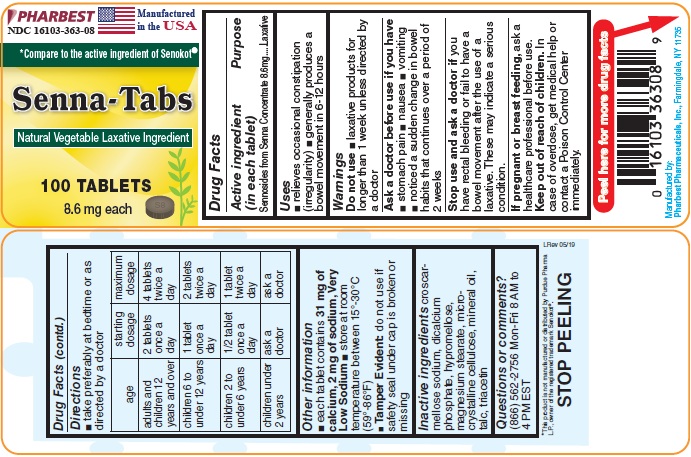 DRUG LABEL: Senna Tabs
NDC: 16103-363 | Form: TABLET, FILM COATED
Manufacturer: Pharbest Pharmaceuticals, Inc.
Category: otc | Type: HUMAN OTC DRUG LABEL
Date: 20251224

ACTIVE INGREDIENTS: SENNOSIDES A AND B 8.6 mg/1 1
INACTIVE INGREDIENTS: CROSCARMELLOSE SODIUM; CALCIUM PHOSPHATE, DIBASIC, ANHYDROUS; HYPROMELLOSES; MAGNESIUM STEARATE; CELLULOSE, MICROCRYSTALLINE; MINERAL OIL; TALC; TRIACETIN

Drug Facts

Active ingredient (in each tablet)

Sennosides from Senna Concentrate 8.6mg

Purpose

Laxative

Uses

- relieves occasional constipation (irregularity)
- generally produces a bowel movement in 6-12 hours

Warnings

Do not use

- laxative products for longer than 1 week unless directed by a doctor

Ask a doctor before use if you have

- stomach pain
- nausea
- vomiting
- noticed a sudden change in bowel habits that continues over a period of 2 weeks

Stop use and ask a doctor if

you have rectal bleeding or fail to have a bowel movement after the use of a laxative.

These may indicate a serious condition.

If pregnant or breast feeding,

ask a health professional before use.

Keep out of reach of children.

In case of overdose, get medical help or contact a Poison Control Center right away.

Directions

- take preferably at bedtime or as directed by a doctor

age | starting dosage | maximum dosage
Adults and children 12 years and over | 2 tablets once a day | 4 tablets twice a day
Children 6 to under 12 years | 1 tablet once a day | 2 tablets twice a day
Children 2 to under 6 years | ½ tablet once a day | 1 tablet twice a day
Children under 2 years | Ask a doctor | Ask a doctor

Other information

- Tamper Evident: Do not use if safetyseal under cap is broken or missing
- each tablet contains 31 mg of calcium, 2 mg of sodium, Very Low Sodium
- store at room temperature between 15^0-30^0C (59^0-86^0F)

Inactive ingredients

croscarmellose sodium, dicalcium phosphate, hypromellose, magnesium stearate, microcrystalline cellulose, mineral oil, talc and triacetin

Questions or comments?

(866) 562-2756 Mon - Fri 8 AM to 4 PM EST

PACKAGE LABEL

PHARBEST

NDC 16103-363-08

manufactured in the USA

*Compare to the active ingredient of Senokot®

Senna-Tabs

Natural Vegetable Laxative Ingredient

100 TABLETS

8.6 mg each